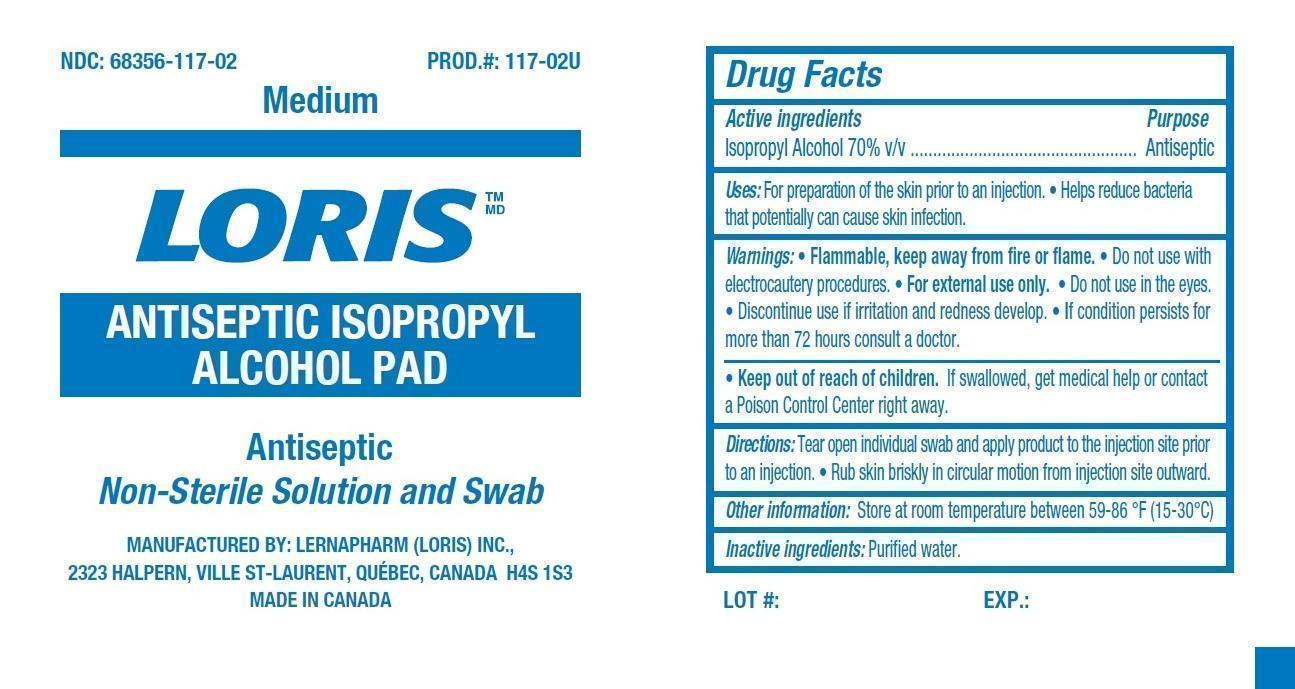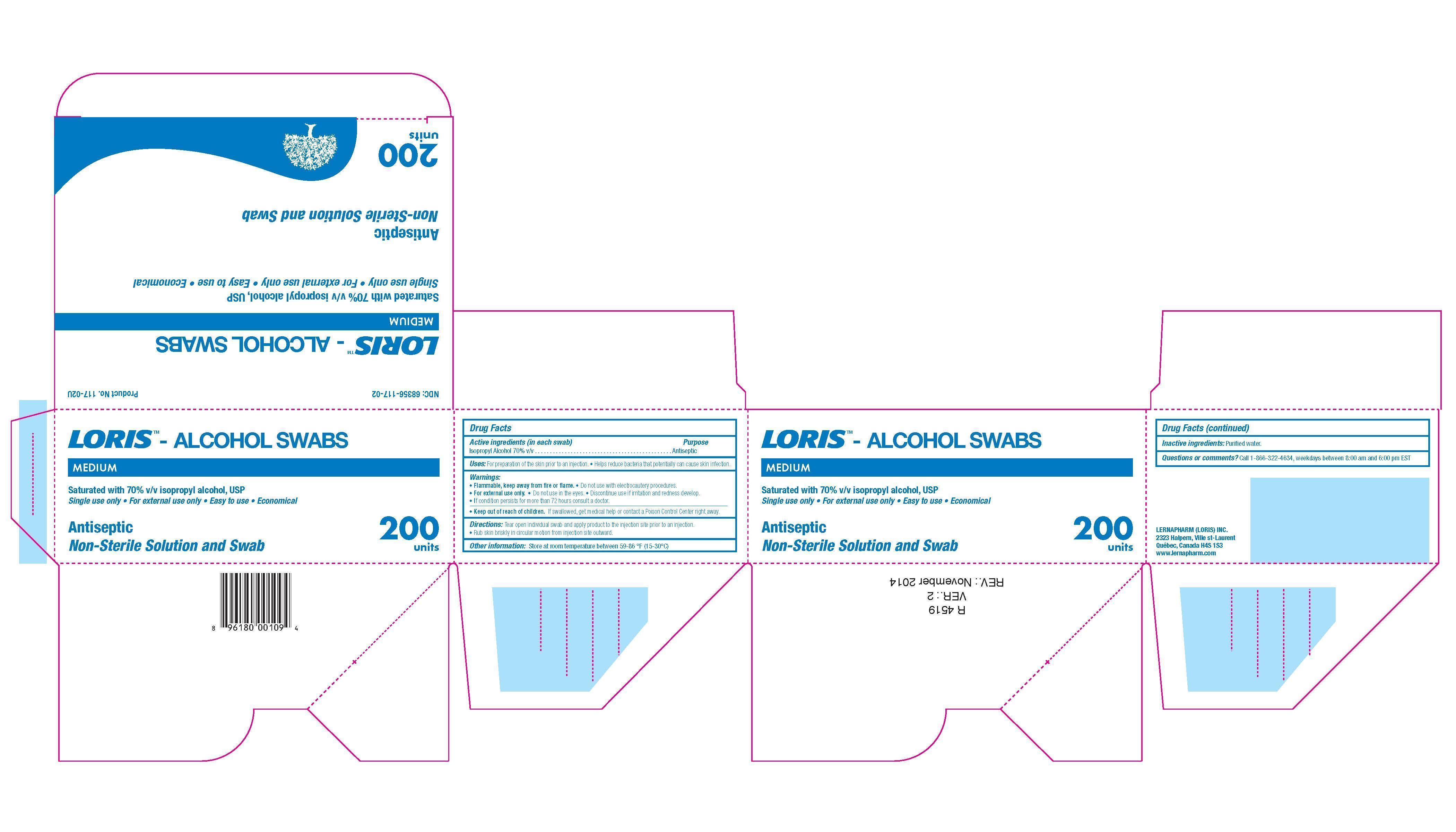 DRUG LABEL: ISOPROPYL ALCOHOL
NDC: 68356-117 | Form: SWAB
Manufacturer: LernaPharm Loris Inc.
Category: otc | Type: HUMAN OTC DRUG LABEL
Date: 20231021

ACTIVE INGREDIENTS: ISOPROPYL ALCOHOL 70 mL/100 mL
INACTIVE INGREDIENTS: WATER

Drug Facts

Active Ingredient (in each swab)

Isopropyl Alcohol 70% v/v

Purpose

Antiseptic

Uses

For preparation of the skin prior to an injection. Helps reduce bacteria that potentially can cause skin infection.

Warnings

Flammable, keep away from fire or flame. Do not use with electrocautery procedures. For external use only. Do not use in the eyes. Discontinue use if irritation and redness develop. If condition persists for more than 72 hours consult a doctor.

Keep out of reach of children.

If swallowed, get medical help or contact a Poison Control Center right away.

Directions

Tear open individual swab and apply product to the injection site prior to an injection. Rub skin briskly in circular motion from injection site outward.

Other Information

Store at room temperature between 59 - 86^0F (15 - 30^0C)

Inactive Ingredients

Purified water

Questions or comments?

Call 1-866-322-4634, weekdays between 8:00 am and 6:00 pm EST

Principal Display Panel

NDC 68356-117-02 PRODUCT # 117-02U
LORIS - ALCOHOL SWABS
MEDIUM

Saturated with 70% v/v isopropyl alcohol, USP

Single use only ● For external use only ● Easy to use ● Economical

Antiseptic

Non-Sterile Solution and Swab
200 units